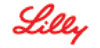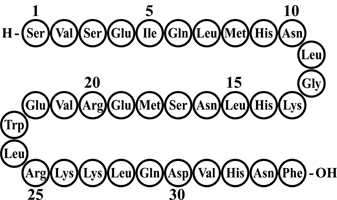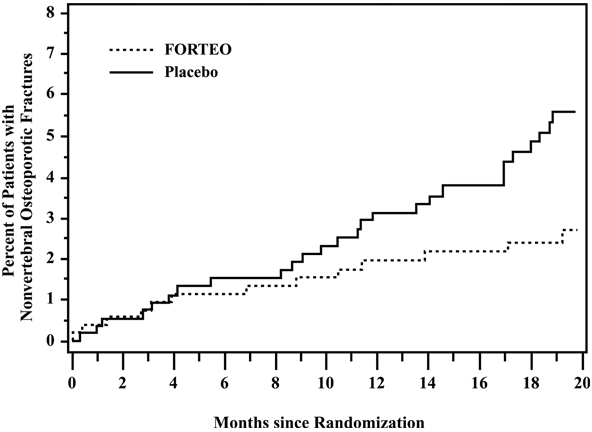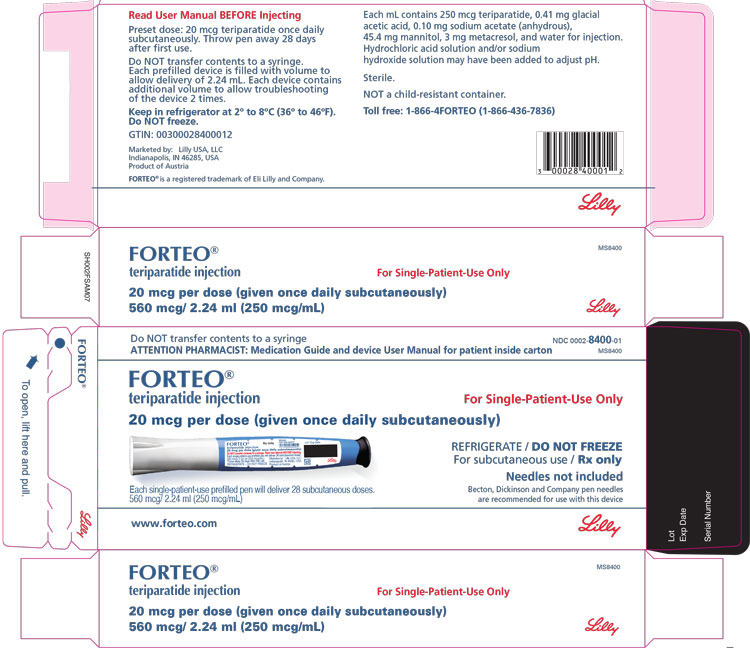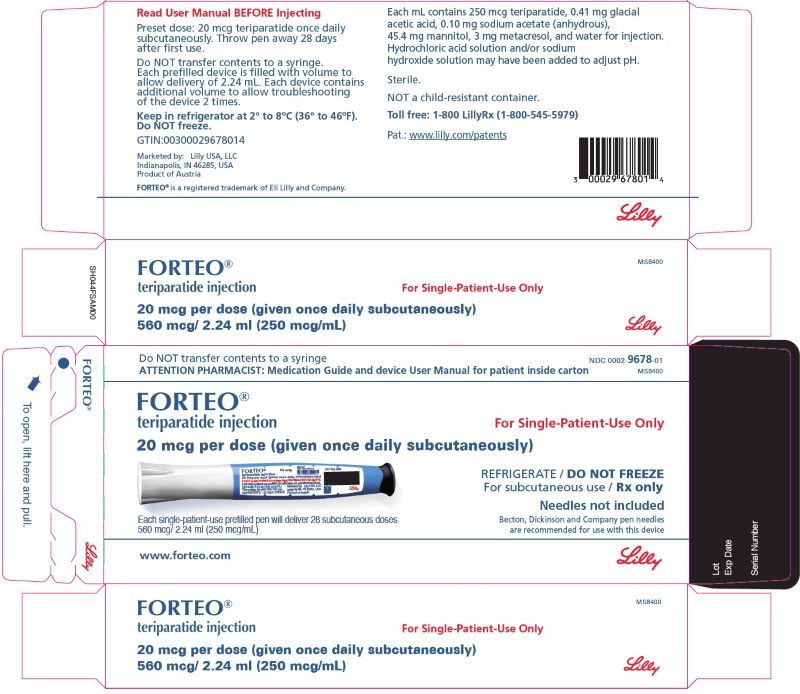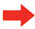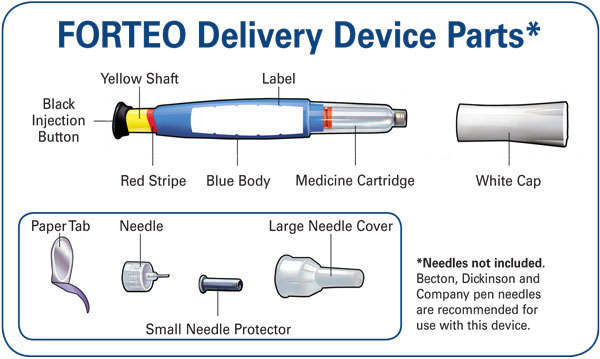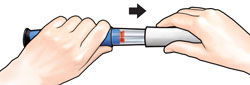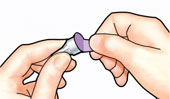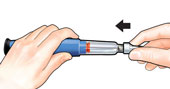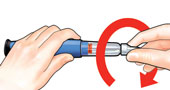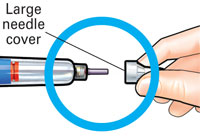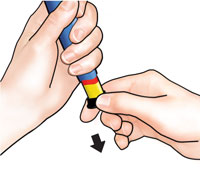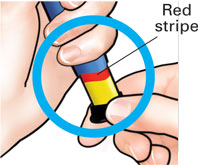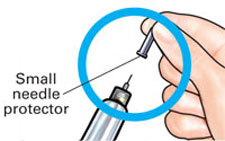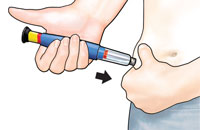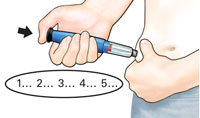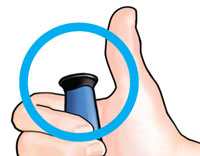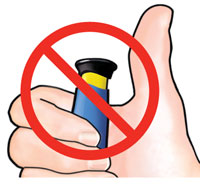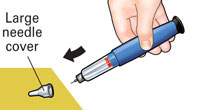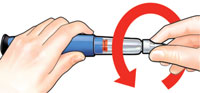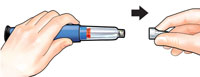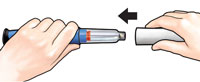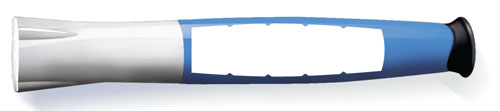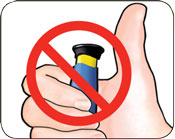 DRUG LABEL: Forteo
NDC: 0002-8400 | Form: INJECTION, SOLUTION
Manufacturer: Eli Lilly and Company
Category: prescription | Type: HUMAN PRESCRIPTION DRUG LABEL
Date: 20250603

ACTIVE INGREDIENTS: Teriparatide 250 ug/1 mL
INACTIVE INGREDIENTS: acetic acid 0.41 mg/1 mL; sodium acetate anhydrous 0.1 mg/1 mL; mannitol 45.4 mg/1 mL; Metacresol 3.0 mg/1 mL; water; hydrochloric acid; sodium hydroxide

HIGHLIGHTS OF PRESCRIBING INFORMATION

These highlights do not include all the information needed to use FORTEO safely and effectively. See full prescribing information for FORTEO.
FORTEO (teriparatide injection), for subcutaneous use
Initial U.S. Approval: 1987

1 INDICATIONS AND USAGE

FORTEO is a parathyroid hormone analog, (PTH 1-34), indicated for:

- Treatment of postmenopausal women with osteoporosis at high risk for fracture or patients who have failed or are intolerant to other available osteoporosis therapy (1)
- Increase of bone mass in men with primary or hypogonadal osteoporosis at high risk for fracture or patients who have failed or are intolerant to other available osteoporosis therapy (1)
- Treatment of men and women with osteoporosis associated with sustained systemic glucocorticoid therapy at high risk for fracture or patients who have failed or are intolerant to other available osteoporosis therapy (1)

2 DOSAGE AND ADMINISTRATION

- Recommended dosage is 20 mcg subcutaneously once a day (2.1)
- Consider supplemental calcium and Vitamin D based on individual patient needs (2.1)
- Administer as a subcutaneous injection into the thigh or abdominal region (2.2)
- Administer initially under circumstances in which the patient can sit or lie down if symptoms of orthostatic hypotension occur (2.2)
- Use of FORTEO for more than 2 years during a patient's lifetime should only be considered if a patient remains at or has returned to having a high risk for fracture (2.3)

3 DOSAGE FORMS AND STRENGTHS

Injection: 560 mcg/2.24 mL (250 mcg/mL) in a single-patient-use prefilled delivery device (pen) intended to deliver 28 daily doses of 20 mcg (3)

4 CONTRAINDICATIONS

- Patients with hypersensitivity to teriparatide or to any of its excipients (4)

5 WARNINGS AND PRECAUTIONS

- Osteosarcoma: Avoid use in patients with increased risk of osteosarcoma including patients with open epiphyses, metabolic bone diseases including Paget's disease, bone metastases or history of skeletal malignancies, prior external beam or implant radiation therapy involving the skeleton, and hereditary disorders predisposing to osteosarcoma. (5.1)
- Hypercalcemia and Cutaneous Calcification: Avoid in patients known to have an underlying hypercalcemic disorder. Discontinue in patients developing worsening of previously stable cutaneous calcification. (5.2)
- Risk of Urolithiasis: Consider the risk/benefit in patients with active or recent urolithiasis because of risk of exacerbation (5.3)
- Orthostatic Hypotension: Transient orthostatic hypotension may occur with initial doses of FORTEO (5.4)

6 ADVERSE REACTIONS

Most common adverse reactions (>10%) include: arthralgia, pain, and nausea (6.1)

To report SUSPECTED ADVERSE REACTIONS, contact Eli Lilly and Company at 1-800-LillyRx (1-800-545-5979) or FDA at 1-800-FDA-1088 or www.fda.gov/medwatch

7 DRUG INTERACTIONS

Digoxin: Transient hypercalcemia may predispose patients to digitalis toxicity (5.5, 7.1)

8 USE IN SPECIFIC POPULATIONS

- Pregnancy: Consider discontinuing when pregnancy is recognized (8.1)
- Lactation: Breastfeeding is not recommended (8.2)
- Pediatric Use: Safety and effectiveness not established. Avoid use due to increased baseline risk of osteosarcoma (5.1, 8.4)

FULL PRESCRIBING INFORMATION

1 INDICATIONS AND USAGE

FORTEO is indicated:

- For the treatment of postmenopausal women with osteoporosis at high risk for fracture (defined herein as having a history of osteoporotic fracture or multiple risk factors for fracture) or who have failed or are intolerant to other available osteoporosis therapy. In postmenopausal women with osteoporosis, FORTEO reduces the risk of vertebral and nonvertebral fractures.
- To increase bone mass in men with primary or hypogonadal osteoporosis at high risk for fracture or who have failed or are intolerant to other available osteoporosis therapy.
- For the treatment of men and women with osteoporosis associated with sustained systemic glucocorticoid therapy (daily dosage equivalent to 5 mg or greater of prednisone) at high risk for fracture or who have failed or are intolerant to other available osteoporosis therapy.

2 DOSAGE AND ADMINISTRATION

2.1 Recommended Dosage

The recommended dosage is 20 mcg per dose given subcutaneously once a day. Instruct patients to take supplemental calcium and vitamin D if daily dietary intake is inadequate.

2.2 Administration Instructions

- Administer FORTEO as a subcutaneous injection into the thigh or abdominal region. FORTEO is not approved for intravenous or intramuscular use.
- FORTEO should be administered initially under circumstances in which the patient can sit or lie down if symptoms of orthostatic hypotension occur [see Warnings and Precautions (5.4)].
- Parenteral drug products should be inspected visually for particulate matter and discoloration prior to administration (FORTEO is a clear and colorless liquid). Do not use if solid particles appear or if the solution is cloudy or colored.
- Patients and/or caregivers who administer FORTEO should receive appropriate training and instruction on the proper use of the FORTEO prefilled delivery device (pen) from a qualified health professional.
- Discard the delivery device 28 days after first use.

2.3 Recommended Treatment Duration

Use of FORTEO for more than 2 years during a patient's lifetime should only be considered if a patient remains at or has returned to having a high risk for fracture [see Warnings and Precautions (5.1)].

3 DOSAGE FORMS AND STRENGTHS

Injection: 560 mcg/2.24 mL (250 mcg/mL) clear, colorless solution in a single-patient-use prefilled delivery device (pen) intended to deliver 28 daily doses of 20 mcg.

4 CONTRAINDICATIONS

FORTEO is contraindicated in patients with hypersensitivity to teriparatide or to any of its excipients. Hypersensitivity reactions have included angioedema and anaphylaxis [see Adverse Reactions (6.3)].

5 WARNINGS AND PRECAUTIONS

5.1 Osteosarcoma

An increase in the incidence of osteosarcoma (a malignant bone tumor) was observed in male and female rats treated with teriparatide. Osteosarcoma has been reported in patients treated with FORTEO in the post marketing setting; however, an increased risk of osteosarcoma has not been observed in observational studies in humans. There are limited data assessing the risk of osteosarcoma beyond 2 years of FORTEO use [see Dosage and Administration (2.3), Adverse Reactions (6.3), and Nonclinical Toxicology (13.1)].

Avoid FORTEO use in patients with (these patients are at increased baseline risk of osteosarcoma):

- Open epiphyses (pediatric and young adult patients) (FORTEO is not approved in pediatric patients) [see Use in Specific Populations (8.4)].
- Metabolic bone diseases other than osteoporosis, including Paget's disease of the bone.
- Bone metastases or a history of skeletal malignancies.
- Prior external beam or implant radiation therapy involving the skeleton.
- Hereditary disorders predisposing to osteosarcoma.

5.2 Hypercalcemia and Cutaneous Calcification

Hypercalcemia

FORTEO has not been studied in patients with pre-existing hypercalcemia. FORTEO may cause hypercalcemia and may exacerbate hypercalcemia in patients with pre-existing hypercalcemia [see Adverse Reactions (6.1, 6.3)]. Avoid FORTEO in patients known to have an underlying hypercalcemic disorder, such as primary hyperparathyroidism.

Risk of Cutaneous Calcification Including Calciphylaxis

Serious reports of calciphylaxis and worsening of previously stable cutaneous calcification have been reported in the post-marketing setting in patients taking FORTEO. Risk factors for development of calciphylaxis include underlying auto-immune disease, kidney failure, and concomitant warfarin or systemic corticosteroid use. Discontinue FORTEO in patients who develop calciphylaxis or worsening of previously stable cutaneous calcification.

5.3 Risk of Urolithiasis

In clinical trials, the frequency of urolithiasis was similar in patients treated with FORTEO and patients treated with placebo. However, FORTEO has not been studied in patients with active urolithiasis. If FORTEO-treated patients have pre-existing hypercalciuria or suspected/known active urolithiasis, consider measuring urinary calcium excretion. Consider the risks and benefits of use in patients with active or recent urolithiasis because of the potential to exacerbate this condition.

5.4 Orthostatic Hypotension

FORTEO should be administered initially under circumstances in which the patient can sit or lie down if symptoms of orthostatic hypotension occur. In short-term clinical pharmacology studies of FORTEO in healthy volunteers, transient episodes of symptomatic orthostatic hypotension were observed in 5% of volunteers. Typically, these events began within 4 hours of dosing and resolved (without treatment) within a few minutes to a few hours. When transient orthostatic hypotension occurred, it happened within the first several doses, it was relieved by placing the person in a reclining position, and it did not preclude continued treatment.

5.5 Risk of Digoxin Toxicity

Hypercalcemia may predispose patients to digitalis toxicity because FORTEO transiently increases serum calcium. Consider the potential onset of signs and symptoms of digitalis toxicity when FORTEO is used in patients receiving digoxin [see Drug Interactions (7.1) and Clinical Pharmacology (12.3)].

6 ADVERSE REACTIONS

6.1 Clinical Trials Experience

Because clinical studies are conducted under widely varying conditions, adverse reaction rates observed in the clinical studies of a drug cannot be directly compared to rates in the clinical studies of another drug and may not reflect the rates observed in practice.

Men with Primary or Hypogonadal Osteoporosis and Postmenopausal Women with Osteoporosis

The safety of FORTEO in the treatment of osteoporosis in men and postmenopausal women was assessed in two randomized, double-blind, placebo-controlled trials of 1382 patients (21% men, 79% women) aged 28 to 86 years (mean 67 years) [see Clinical Studies (14.1, 14.2)]. The median durations of the trials were 11 months for men and 19 months for women, with 691 patients exposed to FORTEO and 691 patients to placebo. All patients received 1000 mg of calcium plus at least 400 IU of vitamin D supplementation per day.

The incidence of all-cause mortality was 1% in the FORTEO group and 1% in the placebo group. The incidence of serious adverse events was 16% in the FORTEO group and 19% in the placebo group. Early discontinuation due to adverse events occurred in 7% in the FORTEO group and 6% in the placebo group.

Table 1 lists adverse events from these two trials that occurred in ≥2% of FORTEO-treated and more frequently than placebo-treated patients.

Table 1: Percentage of Patients with Adverse Events Reported by at Least 2% of FORTEO-Treated Patients and in More FORTEO-Treated Patients than Placebo-Treated Patients from the Two Principal Osteoporosis Trials in Women and Men Adverse Events are Shown Without Attribution of Causality
 | FORTEO N=691 | Placebo N=691
Event Classification | (%) | (%)
Body as a Whole
Pain | 21.3 | 20.5
Headache | 7.5 | 7.4
Asthenia | 8.7 | 6.8
Neck pain | 3.0 | 2.7
Cardiovascular
Hypertension | 7.1 | 6.8
Angina pectoris | 2.5 | 1.6
Syncope | 2.6 | 1.4
Digestive System
Nausea | 8.5 | 6.7
Constipation | 5.4 | 4.5
Diarrhea | 5.1 | 4.6
Dyspepsia | 5.2 | 4.1
Vomiting | 3.0 | 2.3
Gastrointestinal disorder | 2.3 | 2.0
Tooth disorder | 2.0 | 1.3
Musculoskeletal
Arthralgia | 10.1 | 8.4
Leg cramps | 2.6 | 1.3
Nervous System
Dizziness | 8.0 | 5.4
Depression | 4.1 | 2.7
Insomnia | 4.3 | 3.6
Vertigo | 3.8 | 2.7
Respiratory System
Rhinitis | 9.6 | 8.8
Cough increased | 6.4 | 5.5
Pharyngitis | 5.5 | 4.8
Dyspnea | 3.6 | 2.6
Pneumonia | 3.9 | 3.3
Skin and Appendages
Rash | 4.9 | 4.5
Sweating | 2.2 | 1.7

Laboratory Findings

Serum Calcium — FORTEO transiently increased serum calcium, with the maximal effect observed at approximately 4 to 6 hours post-dose. Serum calcium measured at least 16 hours post-dose was not different from pretreatment levels. In clinical trials, the frequency of at least 1 episode of transient hypercalcemia in the 4 to 6 hours after FORTEO administration was 11% of women and 6% of men treated with FORTEO compared to 2% of women and 0% of the men treated with placebo. The percentage of patients treated with FORTEO whose transient hypercalcemia was verified on consecutive measurements was 3% of women and 1% of men.

Urinary Calcium — FORTEO increased urinary calcium excretion, but the frequency of hypercalciuria in clinical trials was similar for patients treated with FORTEO and placebo [see Clinical Pharmacology (12.2)].

Serum Uric Acid — FORTEO increased serum uric acid concentrations. In clinical trials, 3% of FORTEO-treated patients had serum uric acid concentrations above the upper limit of normal compared with 1% of placebo-treated patients. However, the hyperuricemia did not result in an increase in gout, arthralgia, or urolithiasis.

Renal Function — No clinically important adverse renal effects were observed in clinical studies. Assessments included creatinine clearance; measurements of blood urea nitrogen (BUN), creatinine, and electrolytes in serum; urine specific gravity and pH; and examination of urine sediment.

Men and Women with Glucocorticoid-Induced Osteoporosis

The safety of FORTEO in the treatment of men and women with glucocorticoid-induced osteoporosis was assessed in a randomized, double-blind, active-controlled trial of 428 patients (19% men, 81% women) aged 22 to 89 years (mean 57 years) treated with ≥5mg per day prednisone or equivalent for a minimum of 3 months [see Clinical Studies (14.3)]. The duration of the trial was 18 months with 214 patients exposed to FORTEO and 214 patients exposed to an oral daily bisphosphonate (active control). All patients received 1000 mg of calcium plus 800 IU of vitamin D supplementation per day.

There was no increase in mortality in the FORTEO group compared to the active control group. The incidence of serious adverse events was 21% in FORTEO patients and 18% in active control patients, and included pneumonia (3% FORTEO, 1% active control). Early discontinuation because of adverse events occurred in 15% of FORTEO patients and 12% of active control patients, and included dizziness (2% FORTEO, 0% active control).

Adverse events reported at a higher incidence in the FORTEO group and with at least a 2% difference in FORTEO-treated patients compared with active control-treated patients were: nausea (14%, 7%), gastritis (7%, 3%), pneumonia (6%, 3%), dyspnea (6%, 3%), insomnia (5%, 1%), anxiety (4%, 1%), and herpes zoster (3%, 1%), respectively.

6.2 Immunogenicity

As with all peptides, there is potential for immunogenicity. The detection of antibody formation is highly dependent on the sensitivity and specificity of the assay. Additionally, the observed incidence of antibody (including neutralizing antibody) positivity in an assay may be influenced by several factors, including assay methodology, sample handling, timing of sample collection, concomitant medications, and underlying disease. For these reasons, comparison of the incidence of antibodies in the studies described below with the incidence of antibodies in other studies or to other teriparatide products may be misleading.

In the clinical trial of postmenopausal women with osteoporosis [see Clinical Studies (14.1)], antibodies that cross reacted with teriparatide were detected in 3% of women (15/541) who received FORTEO. Generally, antibodies were first detected following 12 months of treatment and diminished after withdrawal of therapy. There was no evidence of hypersensitivity reactions among these patients. Antibody formation did not appear to have effects on serum calcium, or on bone mineral density (BMD) response.

6.3 Postmarketing Experience

Adverse Reactions from Postmarketing Spontaneous Reports

The following adverse reactions have been identified during postapproval use of FORTEO. Because these reactions are reported voluntarily from a population of uncertain size, it is not always possible to reliably estimate their frequency or establish a causal relationship to drug exposure.

- Cases of bone tumor and osteosarcoma have been reported rarely in the postmarketing period [see Warnings and Precautions (5.2)].
- Hypercalcemia greater than 13 mg/dL has been reported with FORTEO use.

Adverse events reported since market introduction that were temporally related to FORTEO therapy include the following:

- Allergic Reactions: Anaphylactic reactions, drug hypersensitivity, angioedema, urticaria
- Investigations: Hyperuricemia
- Respiratory System: Acute dyspnea, chest pain
- Musculoskeletal: Muscle spasms of the leg or back
- Other: Injection site reactions including injection site pain, swelling and bruising; oro-facial edema

Adverse Reactions from Observational Studies to Assess Incidence of Osteosarcoma

Two osteosarcoma surveillance safety studies (U.S. claims-based database studies) were designed to obtain data on the incidence rate of osteosarcoma among FORTEO-treated patients. In these two studies, three and zero osteosarcoma cases were identified among 379,283 and 153,316 FORTEO users, respectively. The study results suggest a similar risk for osteosarcoma between FORTEO users and their comparators. However, the interpretation of the study results calls for caution owing to the limitations of the data sources which do not allow for complete measurement and control for confounders.

7 DRUG INTERACTIONS

7.1 Digoxin

Sporadic case reports have suggested that hypercalcemia may predispose patients to digitalis toxicity. FORTEO may transiently increase serum calcium. Consider the potential onset of signs and symptoms of digitalis toxicity when FORTEO is used in patients receiving digoxin [see Warnings and Precaution (5.5) and Clinical Pharmacology (12.3)].

8 USE IN SPECIFIC POPULATIONS

8.1 Pregnancy

Risk Summary

There are no available data on FORTEO use in pregnant women to evaluate for drug-associated risk of major birth defects, miscarriage, or adverse maternal or fetal outcomes. Consider discontinuing FORTEO when pregnancy is recognized.

In animal reproduction studies, teriparatide increased skeletal deviations and variations in mouse offspring at subcutaneous doses equivalent to more than 60 times the recommended 20 mcg human daily dose (based on body surface area, mcg/m^2), and produced mild growth retardation and reduced motor activity in rat offspring at subcutaneous doses equivalent to more than 120 times the human dose (see Data).

The background risk of major birth defects and miscarriage for the indicated population is unknown. The background risk in the US general population of major birth defects is 2% to 4% and of miscarriage is 15% to 20% of clinically recognized pregnancies.

Data

Animal Data

In animal reproduction studies, pregnant mice received teriparatide during organogenesis at subcutaneous doses equivalent to 8 to 267 times the human dose (based on body surface area, mcg/m^2). At subcutaneous doses ≥60 times the human dose, the fetuses showed an increased incidence of skeletal deviations or variations (interrupted rib, extra vertebra or rib). When pregnant rats received teriparatide during organogenesis at subcutaneous doses 16 to 540 times the human dose, the fetuses showed no abnormal findings.

In a perinatal/postnatal study in pregnant rats dosed subcutaneously from organogenesis through lactation, mild growth retardation was observed in female offspring at doses ≥120 times the human dose. Mild growth retardation in male offspring and reduced motor activity in both male and female offspring were observed at maternal doses of 540 times the human dose. There were no developmental or reproductive effects in mice or rats at doses 8 or 16 times the human dose, respectively.

8.2 Lactation

Risk Summary

It is not known whether teriparatide is excreted in human milk, affects human milk production, or has effects on the breastfed infant. Avoid FORTEO use in women who are breastfeeding.

8.4 Pediatric Use

The safety and effectiveness of FORTEO have not been established in pediatric patients. Pediatric patients are at higher baseline risk of osteosarcoma because of open epiphyses [see Warnings and Precautions (5.1)].

8.5 Geriatric Use

Of the patients who received FORTEO in the osteoporosis trial of 1637 postmenopausal women, 75% were 65 years of age and older and 23% were 75 years of age and older. Of the patients who received FORTEO in the trial of 437 men with primary or hypogonadal osteoporosis, 39% were 65 years of age and over and 13% were 75 years of age and over. Of the 214 patients who received FORTEO in the glucocorticoid induced osteoporosis trial, 28% were 65 years of age and older and 9% were 75 years of age and older. No overall differences in safety or effectiveness of FORTEO have been observed between patients 65 years of age and older and younger adult patients.

8.6 Hepatic Impairment

No studies have been performed in patients with hepatic impairment [see Clinical Pharmacology (12.3)].

8.7 Renal Impairment

In 5 patients with severe renal impairment (CrCl<30 mL/minute), the AUC and T1/2 of teriparatide were increased by 73% and 77%, respectively. Maximum serum concentration of teriparatide was not increased. It is unknown whether FORTEO alters the underlying metabolic bone disease seen in chronic renal impairment [see Clinical Pharmacology (12.3)].

10 OVERDOSAGE

In postmarketing spontaneous reports, there have been cases of medication errors in which the entire contents (up to 800 mcg) (40 times the recommended dose) of the FORTEO prefilled delivery device (pen) have been administered as a single dose. Transient events reported have included nausea, weakness/lethargy and hypotension. No fatalities associated with overdose have been reported. Additional signs, symptoms, and complications of FORTEO overdosage may include a delayed hypercalcemic effect, vomiting, dizziness, and headache.

Overdose Management — There is no specific antidote for a FORTEO overdosage. Treatment of suspected overdosage should include discontinuation of FORTEO, monitoring of serum calcium and phosphorus, and implementation of appropriate supportive measures, such as hydration.

11 DESCRIPTION

FORTEO (teriparatide injection) is a recombinant human parathyroid hormone analog (PTH 1-34). It has an identical sequence to the 34 N-terminal amino acids (the biologically active region) of the 84-amino acid human parathyroid hormone.

The molecular formula of teriparatide is C181H291N55O51S2 and molecular weight is 4117.8 daltons. Its amino acid sequence is shown below:

Teriparatide is manufactured using a strain of Escherichia coli modified by recombinant DNA technology.

FORTEO is supplied as a sterile, colorless, clear, isotonic solution in a glass cartridge which is pre-assembled into a single-patient-use delivery device (pen) for subcutaneous injection. Each delivery device (pen) is filled with volume to allow delivery of 2.24 mL. Each mL contains 250 mcg of teriparatide (as a free base), 0.41 mg of glacial acetic acid, 0.1 mg of sodium acetate (anhydrous), 45.4 mg of mannitol, 3 mg of Metacresol, and Water for Injection. In addition, hydrochloric acid solution 10% and/or sodium hydroxide solution 10% may have been added to adjust the pH to 4.

Each prefilled delivery device (pen) delivers 20 mcg of teriparatide per dose for up to 28 days. Each device contains additional volume to allow troubleshooting of the device 2 times.

12 CLINICAL PHARMACOLOGY

12.1 Mechanism of Action

Endogenous 84-amino acid parathyroid hormone (PTH) is the primary regulator of calcium and phosphate metabolism in bone and kidney. Physiological actions of PTH include regulation of bone metabolism, renal tubular reabsorption of calcium and phosphate, and intestinal calcium absorption. The biological actions of PTH and teriparatide are mediated through binding to specific high-affinity cell-surface receptors. Teriparatide and the 34 N-terminal amino acids of PTH bind to these receptors with the same affinity and have the same physiological actions on bone and kidney. Teriparatide is not expected to accumulate in bone or other tissues.

The skeletal effects of teriparatide depend upon the pattern of systemic exposure. Once-daily administration of teriparatide stimulates new bone formation on trabecular and cortical (periosteal and/or endosteal) bone surfaces by preferential stimulation of osteoblastic activity over osteoclastic activity. In monkey studies, teriparatide improved trabecular microarchitecture and increased bone mass and strength by stimulating new bone formation in both cancellous and cortical bone. In humans, the anabolic effects of teriparatide manifest as an increase in skeletal mass, an increase in markers of bone formation and resorption, and an increase in bone strength. By contrast, continuous excess of endogenous PTH, as occurs in hyperparathyroidism, may be detrimental to the skeleton because bone resorption may be stimulated more than bone formation.

12.2 Pharmacodynamics

Pharmacodynamics in Men with Primary or Hypogonadal Osteoporosis and Postmenopausal Women with Osteoporosis

Effects on Mineral Metabolism — Teriparatide affects calcium and phosphorus metabolism in a pattern consistent with the known actions of endogenous PTH (e.g., increases serum calcium and decreases serum phosphorus).

Serum Calcium Concentrations — When teriparatide 20 mcg was administered once daily, the serum calcium concentration increased transiently, beginning approximately 2 hours after dosing and reaching a maximum concentration between 4 and 6 hours (median increase, 0.4 mg/dL). The serum calcium concentration began to decline approximately 6 hours after dosing and returned to baseline by 16 to 24 hours after each dose.

In a clinical study of postmenopausal women with osteoporosis, the median peak serum calcium concentration measured 4 to 6 hours after dosing with FORTEO (20 mcg subcutaneous once daily) was 9.68 mg/dL at 12 months. The peak serum calcium remained below 11 mg/dL in >99% of women at each visit. Sustained hypercalcemia was not observed.

In this study, 11.1% of women treated with FORTEO had at least 1 serum calcium value above the upper limit of normal (ULN) (10.6 mg/dL) compared with 1.5% of women treated with placebo. The percentage of women treated with FORTEO whose serum calcium was above the ULN on consecutive 4- to 6-hour post-dose measurements was 3% compared with 0.2% of women treated with placebo. In these women, calcium supplements and/or FORTEO doses were reduced. The timing of these dose reductions was at the discretion of the investigator. FORTEO dose adjustments were made at varying intervals after the first observation of increased serum calcium (median 21 weeks). During these intervals, there was no evidence of progressive increases in serum calcium.

In a clinical study of men with either primary or hypogonadal osteoporosis, the effects on serum calcium were similar to those observed in postmenopausal women. The median peak serum calcium concentration measured 4 to 6 hours after dosing with FORTEO was 9.44 mg/dL at 12 months. The peak serum calcium remained below 11 mg/dL in 98% of men at each visit. Sustained hypercalcemia was not observed.

In this study, 6% of men treated with FORTEO daily had at least 1 serum calcium value above the ULN (10.6 mg/dL) compared with none of the men treated with placebo. The percentage of men treated with FORTEO whose serum calcium was above the ULN on consecutive measurements was 1.3% (2 men) compared with none of the men treated with placebo. Calcium supplementation was reduced in these men [see Warnings and Precautions (5.2) and Adverse Reactions (6.1)].

In a clinical study of women previously treated for 18 to 39 months with raloxifene (n=26) or alendronate (n=33), mean serum calcium >12 hours after FORTEO treatment was increased by 0.36 to 0.56 mg/dL, after 1 to 6 months of FORTEO treatment compared with baseline. Of the women pretreated with raloxifene, 3 (11.5%) had a serum calcium >11 mg/dL, and of those pretreated with alendronate, 3 (9.1%) had a serum calcium >11 mg/dL. The highest serum calcium reported was 12.5 mg/dL. None of the women had symptoms of hypercalcemia. There were no placebo controls in this study.

In the study of patients with glucocorticoid-induced osteoporosis, the effects of FORTEO on serum calcium were similar to those observed in postmenopausal women with osteoporosis not taking glucocorticoids.

Urinary Calcium Excretion — In a clinical study of postmenopausal women with osteoporosis who received 1000 mg of supplemental calcium and at least 400 IU of vitamin D, daily FORTEO increased urinary calcium excretion. The median urinary excretion of calcium was 190 mg/day at 6 months and 170 mg/day at 12 months. These levels were 30 mg/day and 12 mg/day higher, respectively, than in women treated with placebo. The incidence of hypercalciuria (>300 mg/day) was similar in the women treated with FORTEO or placebo.

In a clinical study of men with either primary or hypogonadal osteoporosis who received 1000 mg of supplemental calcium and at least 400 IU of vitamin D, daily FORTEO had inconsistent effects on urinary calcium excretion. The median urinary excretion of calcium was 220 mg/day at 1 month and 210 mg/day at 6 months. These levels were 20 mg/day higher and 8 mg/day lower, respectively, than in men treated with placebo. The incidence of hypercalciuria (>300 mg/day) was similar in the men treated with FORTEO or placebo.

Phosphorus and Vitamin D — In single-dose studies, teriparatide produced transient phosphaturia and mild transient reductions in serum phosphorus concentration. However, hypophosphatemia (<2.4 mg/dL) was not observed in clinical trials with FORTEO.

In clinical trials of daily FORTEO, the median serum concentration of 1,25-dihydroxyvitamin D was increased at 12 months by 19% in women and 14% in men, compared with baseline. In the placebo group, this concentration decreased by 2% in women and increased by 5% in men. The median serum 25-hydroxyvitamin D concentration at 12 months was decreased by 19% in women and 10% in men compared with baseline. In the placebo group, this concentration was unchanged in women and increased by 1% in men.

In the study of patients with glucocorticoid-induced osteoporosis, the effects of FORTEO on serum phosphorus were similar to those observed in postmenopausal women with osteoporosis not taking glucocorticoids.

Effects on Markers of Bone Turnover — Daily administration of FORTEO to men and postmenopausal women with osteoporosis in clinical studies stimulated bone formation, as shown by increases in the formation markers serum bone-specific alkaline phosphatase (BSAP) and procollagen I carboxy-terminal propeptide (PICP). Data on biochemical markers of bone turnover were available for the first 12 months of treatment. Peak concentrations of PICP at 1 month of treatment were approximately 41% above baseline, followed by a decline to near-baseline values by 12 months. BSAP concentrations increased by 1 month of treatment and continued to rise more slowly from 6 through 12 months. The maximum increases of BSAP were 45% above baseline in women and 23% in men. After discontinuation of therapy, BSAP concentrations returned toward baseline. The increases in formation markers were accompanied by secondary increases in the markers of bone resorption: urinary N-telopeptide (NTX) and urinary deoxypyridinoline (DPD), consistent with the physiological coupling of bone formation and resorption in skeletal remodeling. Changes in BSAP, NTX, and DPD were lower in men than in women, possibly because of lower systemic exposure to teriparatide in men.

In the study of patients with glucocorticoid-induced osteoporosis, the effects of FORTEO on serum markers of bone turnover were similar to those observed in postmenopausal women with osteoporosis not taking glucocorticoids.

12.3 Pharmacokinetics

Absorption — Teriparatide is absorbed after subcutaneous injection; the absolute bioavailability is approximately 95% based on pooled data from 20-, 40-, and 80- mcg doses (1-, 2-, and 4- times the recommended dosage, respectively). The peptide reaches peak serum concentrations about 30 minutes after subcutaneous injection of a 20-mcg dose and declines to non-quantifiable concentrations within 3 hours.

Distribution — Volume of distribution following intravenous injection is approximately 0.12 L/kg.

Elimination — Systemic clearance of teriparatide (approximately 62 L/hour in women and 94 L/hour in men) exceeds the rate of normal liver plasma flow, consistent with both hepatic and extra-hepatic clearance. The half-life of teriparatide in serum was approximately 1 hour when administered by subcutaneous injection.

No metabolism or excretion studies have been performed with teriparatide. Peripheral metabolism of PTH is believed to occur by non-specific enzymatic mechanisms in the liver followed by excretion via the kidneys.

Specific Populations

Geriatric Patients — No age-related differences in teriparatide pharmacokinetics were detected (range 31 to 85 years).

Male and Female Patients — Although systemic exposure to teriparatide was approximately 20% to 30% lower in men than women, the recommended dosage for men and women is the same.

Racial Groups — The influence of race has not been determined.

Patients with Renal Impairment — No pharmacokinetic differences were identified in 11 patients with creatinine clearance (CrCl) 30 to 72 mL/minute administered a single dose of teriparatide. In 5 patients with severe renal impairment (CrCl<30 mL/minute), the AUC and T1/2 of teriparatide were increased by 73% and 77%, respectively. Maximum serum concentration of teriparatide was not increased. No studies have been performed in patients undergoing dialysis for chronic renal failure.

Patients with Hepatic Impairment — No studies have been performed in patients with hepatic impairment. Non-specific proteolytic enzymes in the liver (possibly Kupffer cells) cleave PTH(1-34) and PTH(1-84) into fragments that are cleared from the circulation mainly by the kidney.

Drug Interaction Studies

Digoxin — In a study of 15 healthy people administered digoxin daily to steady state, a single FORTEO dose did not alter the effect of digoxin on the systolic time interval (from electrocardiographic Q-wave onset to aortic valve closure, a measure of digoxin's calcium-mediated cardiac effect).

Hydrochlorothiazide — In a study of 20 healthy people, the coadministration of hydrochlorothiazide 25 mg with 40 mcg of FORTEO (2 times the recommended dose) did not affect the serum calcium response to FORTEO. The 24-hour urine excretion of calcium was reduced by a clinically unimportant amount (15%). The effect of coadministration of a higher dose of hydrochlorothiazide with FORTEO on serum calcium levels has not been studied.

Furosemide — In a study of 9 healthy people and 17 patients with CrCl 13 to 72 mL/minute, coadministration of intravenous furosemide (20 to 100 mg) with FORTEO 40 mcg (2 times the recommended dose) resulted in small increases in the serum calcium (2%) and 24-hour urine calcium (37%); however, these changes did not appear to be clinically important.

13 NONCLINICAL TOXICOLOGY

13.1 Carcinogenesis, Mutagenesis, Impairment of Fertility

Carcinogenesis

Two carcinogenicity bioassays were conducted in Fischer 344 rats. In the first study, male and female rats were given daily subcutaneous teriparatide injections of 5, 30, or 75 mcg/kg/day for 24 months from 2 months of age. These doses resulted in rat systemic exposures that were 3, 20, and 60 times higher than the systemic exposure observed in humans, respectively, following a subcutaneous dose of 20 mcg (based on AUC comparison). Teriparatide treatment resulted in a marked dose-related increase in the incidence of osteosarcoma, a rare malignant bone tumor, in both male and female rats. Osteosarcomas were observed at all doses and the incidence reached 40% to 50% in the high-dose groups. Teriparatide also caused a dose-related increase in osteoblastoma and osteoma in both sexes. No osteosarcomas, osteoblastomas or osteomas were observed in untreated control rats. The bone tumors in rats occurred in association with a large increase in bone mass and focal osteoblast hyperplasia.

The second 2-year study was carried out in order to determine the effect of treatment duration and animal age on the development of bone tumors. Female rats were treated for different periods between 2 and 26 months of age with subcutaneous teriparatide doses of 5 and 30 mcg/kg (equivalent to 3 and 20 times the human exposure at the 20-mcg dose, respectively, based on AUC comparison). The study showed that the occurrence of osteosarcoma, osteoblastoma and osteoma was dependent upon dose and duration of teriparatide exposure. Bone tumors were observed when immature 2-month old rats were treated with 30 mcg/kg/day of teriparatide for 24 months or with 5 or 30 mcg/kg/day of teriparatide for 6 months. Bone tumors were also observed when mature 6-month old rats were treated with 30 mcg/kg/day of teriparatide for 6 or 20 months. Tumors were not detected when mature 6-month old rats were treated with 5 mcg/kg/day of teriparatide for 6 or 20 months. The results did not demonstrate a difference in susceptibility to bone tumor formation, associated with teriparatide treatment, between mature and immature rats.

No bone tumors were detected in a long-term monkey study [see Nonclinical Toxicology (13.2)].

Mutagenesis

Teriparatide was not genotoxic in any of the following test systems: the Ames test for bacterial mutagenesis; the mouse lymphoma assay for mammalian cell mutation; the chromosomal aberration assay in Chinese hamster ovary cells, with and without metabolic activation; and the in vivo micronucleus test in mice.

Impairment of Fertility

No effects on fertility were observed in male and female rats given subcutaneous teriparatide doses of 30, 100, or 300 mcg/kg/day prior to mating and in females continuing through gestation Day 6 (16 to 160 times the human dose of 20 mcg based on surface area, mcg/m^2).

13.2 Animal Toxicology

In single-dose rodent studies using subcutaneous injection of teriparatide, no mortality was seen in rats given doses of 1000 mcg/kg (540 times the human dose based on surface area, mcg/m^2) or in mice given 10,000 mcg/kg (2700 times the human dose based on surface area, mcg/m^2).

In a long-term study, skeletally mature ovariectomized female monkeys (N=30 per treatment group) were given either daily subcutaneous teriparatide injections of 5 mcg/kg or vehicle. Following the 18-month treatment period, the monkeys were removed from teriparatide treatment and were observed for an additional 3 years. The 5 mcg/kg dose resulted in systemic exposures that were approximately 6 times higher than the systemic exposure observed in humans following a subcutaneous dose of 20 mcg (based on AUC comparison). Bone tumors were not detected by radiographic or histologic evaluation in any monkey in the study.

14 CLINICAL STUDIES

14.1 Treatment of Osteoporosis in Postmenopausal Women

The safety and efficacy of once-daily FORTEO, median exposure of 19 months, were examined in a double-blind, multicenter, placebo-controlled clinical study of 1637 postmenopausal women with osteoporosis. In this study 541 postmenopausal women were treated with 20 mcg FORTEO subcutaneously once daily.

All women received 1000 mg of calcium and at least 400 IU of vitamin D per day. Baseline and endpoint spinal radiographs were evaluated using the semiquantitative scoring. Ninety percent of the women in the study had 1 or more radiographically diagnosed vertebral fractures at baseline. The primary efficacy endpoint was the occurrence of new radiographically diagnosed vertebral fractures defined as changes in the height of previously undeformed vertebrae. Such fractures are not necessarily symptomatic.

Effect on Fracture Incidence

New Vertebral Fractures — FORTEO, when taken with calcium and vitamin D and compared with calcium and vitamin D alone, reduced the risk of 1 or more new vertebral fractures from 14.3% of women in the placebo group to 5.0% in the FORTEO group (444 of the 541 patients treated with 20 mcg once daily of FORTEO were included in this analysis). This difference was statistically significant (p<0.001); the absolute reduction in risk was 9.3% and the relative reduction was 65%. FORTEO was effective in reducing the risk for vertebral fractures regardless of age, baseline rate of bone turnover, or baseline BMD (see Table 2).

Table 2: Effect of FORTEO on Risk of Vertebral Fractures in Postmenopausal Women with Osteoporosis
Percent of Women With Fracture
 | FORTEO (N=444) | Placebo (N=448) | Absolute Risk Reduction (%, 95% CI) | Relative Risk Reduction (%, 95% CI)
New fracture (≥1) | 5.0a | 14.3 | 9.3 (5.5-13.1) | 65 (45-78)
1 fracture | 3.8 | 9.4
2 fractures | 0.9 | 2.9
≥3 fractures | 0.2 | 2.0
a p≤0.001 compared with placebo.

New Nonvertebral Osteoporotic Fractures — FORTEO significantly reduced the risk of any nonvertebral fracture from 5.5% in the placebo group to 2.6% in the FORTEO group (p<0.05). The absolute reduction in risk was 2.9% and the relative reduction was 53%. The incidence of new nonvertebral fractures in the FORTEO group compared with the placebo group was ankle/foot (0.2%, 0.7%), hip (0.2%, 0.7%), humerus (0.4%, 0.4%), pelvis (0%, 0.6%), ribs (0.6%, 0.9%), wrist (0.4%, 1.3%), and other sites (1.1%, 1.5%), respectively.

The cumulative percentage of postmenopausal women with osteoporosis who sustained new nonvertebral fractures was lower in women treated with FORTEO than in women treated with placebo (see Figure 1).

Figure 1: Cumulative Percentage of Postmenopausal Women with Osteoporosis Sustaining New Nonvertebral Osteoporotic Fractures

Effect on Bone Mineral Density (BMD)

FORTEO increased lumbar spine BMD in postmenopausal women with osteoporosis. Statistically significant increases were seen at 3 months and continued throughout the treatment period. Postmenopausal women with osteoporosis who were treated with FORTEO had statistically significant increases in BMD from baseline to endpoint at the lumbar spine, femoral neck, total hip, and total body (see Table 3).

Table 3: Mean Percent Change in BMD from Baseline to Endpointa in Postmenopausal Women with Osteoporosis, Treated with FORTEO or Placebo for a Median of 19 Months
 | FORTEO N=541 | Placebo N=544
Lumbar spine BMD | 9.7b | 1.1
Femoral neck BMD | 2.8c | -0.7
Total hip BMD | 2.6c | -1.0
Trochanter BMD | 3.5c | -0.2
Intertrochanter BMD | 2.6c | -1.3
Ward's triangle BMD | 4.2c | -0.8
Total body BMD | 0.6c | -0.5
Distal 1/3 radius BMD | -2.1 | -1.3
Ultradistal radius BMD | -0.1 | -1.6
a Intent-to-treat analysis, last observation carried forward.
b p<0.001 compared with placebo.
c p<0.05 compared with placebo.

FORTEO treatment increased lumbar spine BMD from baseline in 96% of postmenopausal women treated. Seventy-two percent of patients treated with FORTEO achieved at least a 5% increase in spine BMD, and 44% gained 10% or more.

Both treatment groups lost height during the trial. The mean decreases were 3.61 and 2.81 mm in the placebo and FORTEO groups, respectively.

Bone Histology

The effects of FORTEO on bone histology were evaluated in iliac crest biopsies of 35 postmenopausal women treated for 12 to 24 months with calcium and vitamin D and FORTEO. Normal mineralization was observed with no evidence of cellular toxicity. The new bone formed with FORTEO was of normal quality (as evidenced by the absence of woven bone and marrow fibrosis).

14.2 Treatment to Increase Bone Mass in Men with Primary or Hypogonadal Osteoporosis

The safety and efficacy of once-daily FORTEO, median exposure of 10 months, were examined in a double-blind, multicenter, placebo-controlled clinical study of 437 men with either primary (idiopathic) or hypogonadal osteoporosis. In this study, 151 men received 20 mcg of FORTEO given subcutaneously once daily. All men received 1000 mg of calcium and at least 400 IU of vitamin D per day. The primary efficacy endpoint was change in lumbar spine BMD.

FORTEO increased lumbar spine BMD in men with primary or hypogonadal osteoporosis. Statistically significant increases were seen at 3 months and continued throughout the treatment period. FORTEO was effective in increasing lumbar spine BMD regardless of age, baseline rate of bone turnover, and baseline BMD. The effects of FORTEO at additional skeletal sites are shown in Table 4.

FORTEO treatment for a median of 10 months increased lumbar spine BMD from baseline in 94% of men treated. Fifty-three percent of patients treated with FORTEO achieved at least a 5% increase in spine BMD, and 14% gained 10% or more.

Table 4: Mean Percent Change in BMD from Baseline to Endpointa in Men with Primary or Hypogonadal Osteoporosis, Treated with FORTEO or Placebo for a Median of 10 Months
 | FORTEO N=151 | Placebo N=147
Lumbar spine BMD | 5.9b | 0.5
Femoral neck BMD | 1.5c | 0.3
Total hip BMD | 1.2 | 0.5
Trochanter BMD | 1.3 | 1.1
Intertrochanter BMD | 1.2 | 0.6
Ward's triangle BMD | 2.8 | 1.1
Total body BMD | 0.4 | -0.4
Distal 1/3 radius BMD | -0.5 | -0.2
Ultradistal radius BMD | -0.5 | -0.3
a Intent-to-treat analysis, last observation carried forward.
b p<0.001 compared with placebo.
c p<0.05 compared with placebo.

14.3 Treatment of Men and Women with Glucocorticoid-Induced Osteoporosis

The efficacy of FORTEO for treating glucocorticoid-induced osteoporosis was assessed in a randomized, double-blind, active-controlled trial of 428 patients (19% men, 81% women) aged 22 to 89 years (mean 57 years) treated with ≥5 mg/day prednisone or equivalent for a minimum of 3 months. The duration of the trial was 18 months. In the trial 214 patients were treated with FORTEO 20 mcg given subcutaneously once daily. In the FORTEO group, the baseline median glucocorticoid dose was 7.5 mg/day and the baseline median duration of glucocorticoid use was 1.5 years. The mean (SD) baseline lumbar spine BMD was 0.85 ± 0.13 g/cm^2 and lumbar spine BMD T-score was –2.5 ± 1 (number of standard deviations below the mean BMD value for healthy adults). A total of 30% of patients had prevalent vertebral fracture(s) and 43% had prior non-vertebral fracture(s). The patients had chronic rheumatologic, respiratory or other diseases that required sustained glucocorticoid therapy. All patients received 1000 mg of calcium plus 800 IU of vitamin D supplementation per day.

Because of differences in mechanism of action (anabolic vs. anti-resorptive) and lack of clarity regarding differences in BMD as an adequate predictor of fracture efficacy, data on the active comparator are not presented.

Effect on Bone Mineral Density (BMD)

In patients with glucocorticoid-induced osteoporosis, FORTEO increased lumbar spine BMD compared with baseline at 3 months through 18 months of treatment. In patients treated with FORTEO, the mean percent change in BMD from baseline to endpoint was 7.2% at the lumbar spine, 3.6% at the total hip, and 3.7% at the femoral neck (p <0.001 all sites). The relative treatment effects of FORTEO were consistent in subgroups defined by gender, age, geographic region, body mass index, underlying disease, prevalent vertebral fracture, baseline glucocorticoid dose, prior bisphosphonate use, and glucocorticoid discontinuation during trial.

16 HOW SUPPLIED/STORAGE AND HANDLING

16.1 How Supplied

FORTEO (teriparatide injection) is a clear and colorless solution, available as single-patient-use prefilled delivery device (pen) in the following package size:

- 560 mcg/2.24 mL (250 mcg/mL) [intended to deliver 28 daily doses of 20 mcg] NDC 0002-9678-01 (MS8400).

16.2 Storage and Handling

- Store FORTEO under refrigeration at 2° to 8°C (36° to 46°F) at all times except when administering the product.
- Recap the delivery device (pen) when not in use to protect the cartridge from physical damage and light.
- When using FORTEO, minimize the time out of the refrigerator; deliver the dose immediately following removal from the refrigerator.
- Do not freeze. Do not use FORTEO if it has been frozen.
- Throw away the device 28 days after first use.

17 PATIENT COUNSELING INFORMATION

Advise the patient to read the FDA-approved patient labeling (Medication Guide and the User Manual) before starting FORTEO and each time the prescription is renewed. Failure to follow the instructions may result in inaccurate dosing.

Osteosarcoma

Patients should be made aware that in rats, teriparatide caused an increase in the incidence of osteosarcoma (a malignant bone tumor). Although cases of osteosarcoma have been reported in patients using FORTEO no increased risk of osteosarcoma was observed in adult humans treated with FORTEO [see Warnings and Precautions (5.1)].

Hypercalcemia

Instruct patients taking FORTEO to contact a health care provider if they develop persistent symptoms of hypercalcemia (e.g., nausea, vomiting, constipation, lethargy, muscle weakness) [see Warnings and Precautions (5.2)].

Orthostatic Hypotension

When initiating FORTEO treatment, instruct patients to be prepared to immediately sit or lie down during or after administration in case they feel lightheaded or have palpitations after the injection. Instruct patients to sit or lie down until the symptoms resolve. If symptoms persist or worsen, instruct patients to consult a healthcare provider before continuing treatment [see Warnings and Precautions (5.4)].

Other Osteoporosis Treatment Modalities

Patients should be informed regarding the roles of supplemental calcium and/or vitamin D.

Use of the Prefilled Delivery Device (Pen)

Instruct patients and caregivers who administer FORTEO on how to properly use the delivery device (refer to User Manual), to properly dispose of needles, and not to share their prefilled delivery device with other patients. Instruct patients and caregivers who administer FORTEO that the contents of the delivery device should not be transferred to a syringe.

Inform patients that each FORTEO delivery device can be used up to 28 days after first use. After the 28-day use period, instruct patients to discard the FORTEO delivery device, even if it still contains some unused solution. Instruct patients not to use FORTEO after the expiration date printed on the delivery device and packaging.

Marketed by: Lilly USA, LLC
Indianapolis, IN 46285, USA
www.forteo.com

Pat.: www.lilly.com/patents

Copyright © 2002, 2025, Eli Lilly and Company. All rights reserved.

FOR-0006-USPI-20250603

MEDICATION GUIDE
FORTEO® (for-TAY-o)
teriparatide injection
for subcutaneous use

Read this Medication Guide before you start using FORTEO and each time you get a refill. There may be new information. Also, read the User Manual that comes with the FORTEO delivery device (pen) for information on how to use the device to inject your medicine the right way. This Medication Guide does not take the place of talking with your healthcare provider about your medical condition or your treatment.

What is the most important information I should know about FORTEO?
Possible bone cancer. During drug testing, the medicine in FORTEO caused some rats to develop a bone cancer called osteosarcoma. Studies in people have not shown that FORTEO increases your chance of getting osteosarcoma. There is little information about the chance of getting osteosarcoma in patients using FORTEO beyond 2 years.

What is FORTEO?
FORTEO is a prescription medicine used to:

- treat postmenopausal women who have osteoporosis who are at high risk for having broken bones (fractures) or who cannot use other osteoporosis treatments. FORTEO can lessen the chance of broken bones (fractures) in the spine and other bones in postmenopausal women with osteoporosis.
- increase the bone mass in men with primary or hypogonadal osteoporosis who are at high risk for having broken bones (fractures) or who cannot use other osteoporosis treatments.
- treat both men and women with osteoporosis due to use of glucocorticoid medicines, such as prednisone, for several months, who are at high risk for having broken bones (fractures) or who cannot use other osteoporosis treatments.

It is not known if FORTEO is safe and effective in children.
FORTEO should not be used in children and young adults whose bones are still growing.

Who should not use FORTEO?
Do not use FORTEO if you:

- are allergic to any of the ingredients in FORTEO. See the end of this Medication Guide for a complete list of the ingredients in FORTEO.

Symptoms of a serious allergic reaction of FORTEO may include swelling of the face, lips, tongue or throat that may cause difficulty in breathing or swallowing. Call your healthcare provider right away or get emergency medical help if you get any of these symptoms.

What should I tell my healthcare provider before using FORTEO?
Before you use FORTEO, tell your healthcare provider about all of your medical conditions, including if you:

- have a certain bone disease called Paget's disease or other bone disease.
- have bone cancer or have had a history of bone cancer.
- are a young adult whose bones are still growing.
- have had radiation therapy.
- are affected with a condition that runs in your family that can increase your chance of getting cancer in your bones.
- have or have had too much calcium in your blood (hypercalcemia).
- have or have had a skin condition with painful sores or wounds caused by too much calcium.
- have or have had kidney stones.
- take medicines that contain digoxin.
- are pregnant or plan to become pregnant. It is not known if FORTEO will harm your unborn baby.
- are breastfeeding or plan to breastfeed. It is not known if FORTEO passes into your breastmilk. You should not breastfeed while taking FORTEO.

Tell your healthcare provider about all the medicines you take including prescription and over-the-counter medicines, vitamins, and herbal supplements.
Know the medicines you take. Keep a list of them to show your healthcare provider and pharmacist when you get a new medicine.

How should I use FORTEO?

- Read the detailed Instructions for Use (User Manual) included with your FORTEO delivery device.
- Use FORTEO exactly as your healthcare provider tells you to. Your healthcare provider will tell you how much FORTEO to use and when to use it.
- Before you try to inject FORTEO yourself, a healthcare provider should teach you how to use the FORTEO delivery device to give your injection the right way.
- Inject FORTEO 1 time each day in your thigh or abdomen (lower stomach area). Do not inject into a vein or a muscle. Talk to a healthcare provider about how to rotate injection sites.
- The FORTEO delivery device has enough medicine for 28 days. It is set to give a 20-microgram dose of medicine each day. Do not inject all the medicine in the FORTEO delivery device at any one time.
- Do not transfer the medicine from the FORTEO delivery device to a syringe. This can result in taking the wrong dose of FORTEO. If you do not have pen needles to use with your FORTEO delivery device, talk with your healthcare provider.
- FORTEO should look clear and colorless. Do not use FORTEO if it has particles in it, or if it is cloudy or colored.
- Inject FORTEO right away after you take the delivery device out of the refrigerator.
- After each use, safely remove the needle, recap the delivery device, and put it back in the refrigerator right away.
- When you inject the first few doses of FORTEO, make sure you are in a place where you can sit or lie down right away in case you feel dizzy or have an abnormal heartbeat after the injection.
- Do not take more than 1 injection in the same day.
- Do not share your FORTEO delivery device with other people.
- If you take more FORTEO than prescribed, call your healthcare provider. If you take too much FORTEO, you may have nausea, vomiting, weakness, or dizziness.
- You should not use FORTEO for more than 2 years over your lifetime unless your healthcare provider finds that you need longer treatment because you have a high chance of breaking your bones.

If your healthcare provider recommends calcium and vitamin D supplements, you can take them at the same time you take FORTEO.

What are the possible side effects of FORTEO?
FORTEO may cause serious side effects including:

- See “What is the most important information I should know about FORTEO?”
- Bone cancer (osteosarcoma): Tell your healthcare provider right away if you have pain in your bones, pain in any areas of your body that does not go away, or any new or unusual lumps or swelling under your skin that is tender to touch.
- Increased calcium in your blood. Tell your healthcare provider if you have nausea, vomiting, constipation, low energy, or muscle weakness. These may be signs there is too much calcium in your blood.
- Worsening of your kidney stones. If you have or have had kidney stones your healthcare provider may check the calcium levels in your urine while you use FORTEO to see if there is worsening of this condition.
- Decrease in blood pressure when you change positions. Some people may feel dizzy, get a fast heartbeat, or feel light-headed right after the first few doses of FORTEO. This usually happens within 4 hours of taking FORTEO and goes away within a few hours. For the first few doses, give your injections of FORTEO in a place where you can sit or lie down right away if you get these symptoms. If your symptoms get worse or do not go away, contact your healthcare provider before you continue using FORTEO.

The most common side effects of FORTEO include:

- pain
- nausea
- joint aches

These are not all the possible side effects of FORTEO. For more information, ask your healthcare provider or pharmacist.
Call your doctor for medical advice about side effects. You may report side effects to FDA at 1-800-FDA-1088.

How should I store FORTEO?

- Store FORTEO in the refrigerator between 36°F to 46°F (2°C to 8°C) until ready to use. Use FORTEO right away after you remove it from the refrigerator.
- Do not freeze FORTEO. Do not use FORTEO if it has been frozen.
- Throw away the FORTEO delivery device after 28 days even if it has medicine in it (see the User Manual).
- Do not use FORTEO after the expiration date printed on the delivery device and packaging.
- Recap FORTEO when not in use to protect it from physical damage and light.

Keep FORTEO and all medicines out of the reach of children.

General information about the safe and effective use of FORTEO.
Medicines are sometimes prescribed for purposes other than those listed in a Medication Guide. Do not use FORTEO for a condition for which it was not prescribed. Do not give FORTEO to other people, even if they have the same symptoms that you have. It may harm them.
You can ask your pharmacist or healthcare provider for information about FORTEO that is written for health professionals.

What are the ingredients in FORTEO?
Active ingredient: teriparatide
Inactive ingredients: glacial acetic acid, sodium acetate (anhydrous), mannitol, metacresol, and water for injection. In addition, hydrochloric acid solution 10% and/or sodium hydroxide solution 10% may have been added to adjust the product to pH 4.

For more information, go to www.FORTEO.com or call Lilly at 1-866-436-7836.
Marketed by: Lilly USA, LLC, Indianapolis, IN 46285, USA
Copyright © 2002, 2020, Eli Lilly and Company. All rights reserved.
FOR-0003-MG-20201116

This Medication Guide has been approved by the U.S. Food and Drug Administration.

Revised: 11/2020

INSTRUCTIONS FOR USE

FORTEO® (for-TAY-o)
teriparatide injection

User Manual

Important: First read the Medication Guide that comes inside your FORTEO carton.

Before you use your new FORTEO delivery device, please read the entire front and back of this User Manual completely. Follow the directions carefully when using the FORTEO delivery device.

Do not share your delivery device or needles because infection or disease can be spread from one person to another.

The FORTEO delivery device contains 28 days of medicine. Throw away the FORTEO delivery device 28 days after first use, even if it is not completely empty. Do not inject more than one dose of FORTEO in the same day.

Do not transfer FORTEO to a syringe.

Wash your hands before every injection. Prepare the injection site as your healthcare provider instructed.

1
Pull off white cap

Check the FORTEO delivery device label to make sure you have the right medicine and that it has not expired.
Do not use if the FORTEO delivery device looks damaged, if the medicine in the cartridge is not clear and colorless, or if it has particles in it.

2 Attach new needle
 | Pull off paper tab. | Push needle straight onto medicine cartridge. | Screw on needle clockwise until firmly attached. | Pull off large needle cover and save it.

3 Set dose
 | Pull out black injection button until it stops. If you cannot pull out the black injection button see Troubleshooting, Problem E, on back page. | Check to make sure red stripe shows. | Pull off small needle protector and throw away.

4 Inject dose
 | Gently hold a fold of skin on your thigh or abdomen and insert needle straight into skin. | Push in black injection button until it stops. Hold it in and count to 5 slowly. You must wait until the count of 5 to make sure you receive the correct dose. Then pull the needle from skin.

IMPORTANT
5 Confirm dose |  | After completing the injection: Once the needle is removed from the skin, take your thumb off the black injection button. Check to make sure the black injection button is all the way in. If the yellow shaft does not show, you have finished the injection steps the right way. |  | You should NOT see any of the yellow shaft. If you do and have already injected the medicine, do not inject yourself a second time on the same day. Instead, you MUST reset the FORTEO delivery device (see Troubleshooting, Problem A, on back page).

6 Remove needle
 | Put large needle cover on needle. Do not try to put the needle cover back on with your hands. | Unscrew the covered needle all the way by giving the large needle cover 3 to 5 counter-clockwise turns. | Pull off needle and throw away in a puncture-resistant container. | Push white cap back on. Right after use, place FORTEO delivery device in the refrigerator.

For more information, or if you have any questions, turn to the back of this page.

 |  | FORTEO® (for-TAY-o) teriparatide injection
Troubleshooting
Problem |  |  | Solution
A. The yellow shaft is still showing after I push in the black injection button. How do I reset my FORTEO delivery device? |  |  | To reset the FORTEO delivery device, follow the steps below.; 1. If you have already injected, DO NOT inject yourself a second time on the same day. 2. Remove the needle. 3. Attach a new needle, pull off the large needle cover and save it. 4. Pull out the black injection button until it stops. Check to make sure the red stripe shows. 5. Pull off the small needle protector and throw away. 6. Point the needle down into an empty container. Push in the black injection button until it stops. Hold it in and slowly count to five. You may see a small stream or drop of fluid. When you have finished, the black injection button should be all the way in. 7. If you still see the yellow shaft showing, contact Eli Lilly and Company (see Contact Information below) or your healthcare provider. 8. Put the large needle cover on needle. Unscrew the needle all the way by giving the needle cover 3 to 5 counter-clockwise turns. Pull off the covered needle and throw away as instructed by your healthcare provider. Push the white cap back on, and put your FORTEO delivery device in the refrigerator.
 |  |  | You can prevent this problem by always using a NEW needle for each injection, and by pushing the black injection button all the way in and slowly counting to five.
B. How can I tell if my FORTEO delivery device works? |  |  | The black injection button should be all the way in to show that the full dose of medicine has been injected from the FORTEO delivery device. Use a new needle every time you inject to be sure your FORTEO delivery device will work properly.
C. I see an air bubble in my FORTEO delivery device. |  |  | A small air bubble will not affect your dose and it will not harm you. You can continue to take your dose as usual.
D. I cannot get the needle off. |  |  | 1. Put the large needle cover on the needle. 2. Use the large needle cover to unscrew the needle. 3. Unscrew the needle all the way by giving the large needle cover 3 to 5 counter-clockwise turns. 4. If you still cannot get the needle off, ask someone to help you.
E. What should I do if I have difficulty pulling out the black injection button? |  |  | Change to a new FORTEO delivery device to take your dose as instructed by your healthcare provider. When the black injection button becomes hard to pull out, this means there is not enough medicine in your FORTEO delivery device for another dose. You may still see some medicine left in the cartridge.

Cleaning and Storage

Cleaning Your FORTEO Delivery Device

- Wipe the outside of the FORTEO delivery device with a damp cloth.
- Do not place the FORTEO delivery device in water, or wash or clean it with any liquid.

Storing Your FORTEO Delivery Device

- After each use, refrigerate the FORTEO delivery device right away. Read and follow the instructions in the Medication Guide section “How should I store FORTEO?”.
- Do not store the FORTEO delivery device with a needle attached. Doing this may cause air bubbles to form in the medicine cartridge.
- Store the FORTEO delivery device with the white cap on.
- Do not freeze FORTEO. If the FORTEO delivery device has been frozen, throw the device away and use a new FORTEO delivery device.
- If the FORTEO delivery device has been left out of the refrigerator, do not throw the delivery device away. Place the delivery device back in the refrigerator and call Eli Lilly and Company at 1-800-LillyRx (1-800-545-5979).

Other Important Notes

- The FORTEO delivery device contains 28 days of medicine.
- Each device contains additional volume to allow troubleshooting of the device 2 times.
- Do not transfer FORTEO to a syringe. This may result in you taking the wrong dose of medicine.
- Read and follow the instructions in the User Manual so that you use your FORTEO delivery device the right way.
- Check the FORTEO delivery device label to make sure you have the right medicine and that it has not expired.
- Do not use the FORTEO delivery device if it looks damaged. Look at the FORTEO medicine in the cartridge. If the medicine is not clear and colorless, or if it has particles, do not use it. Call Eli Lilly and Company if you notice any of these (see Contact Information).
- Use a new needle for each injection.
- During injection, you may hear one or more clicks – this is normal.
- The FORTEO delivery device is not recommended for use by the blind or by those who have vision problems without help from a person trained in the proper use of the device.
- Keep your FORTEO delivery device and needles out of the reach of children.

Disposal of Pen Needles and Delivery Device

Disposal of Pen Needles and the FORTEO Delivery Device

- Before throwing away the FORTEO delivery device, be sure to remove the pen needle.
- Throw away your FORTEO delivery device and used needles as instructed by your healthcare provider, local or state laws, or institutional policies.

Dispose of the FORTEO delivery device 28 days after first use.

1st use date ______ / ______ / ______
Throw away after ______ / ______ / ______

Contact Information

If you have questions or need help with your FORTEO delivery device, contact Eli Lilly and Company at 1-800-LillyRx (1-800-545-5979) or your healthcare provider.
For more information about FORTEO, go to www.FORTEO.com.
Marketed by: Lilly USA, LLC
Indianapolis, IN 46285, USA
FORTEO is a registered trademark of Eli Lilly and Company.
® Registered trademarks owned by Eli Lilly and Company; used under license.
Copyright © 2008, 2025, Eli Lilly and Company. All rights reserved.

Literature revised Jun 03, 2025

FOR-0004-IFU-20250603

PACKAGE LABEL

PACKAGE LABEL – FORTEO 20 mcg per dose, 2.24 mL

Do NOT transfer contents to a syringe

ATTENTION PHARMACIST: Medication Guide and device User Manual for patient inside carton

NDC 0002-8400-01

MS8400

FORTEO®

teriparatide injection

20 mcg per dose (given once daily subcutaneously)

Each single-patient-use prefilled pen will deliver 28 subcutaneous doses.

560 mcg/ 2.24 mL (250 mcg/mL)

For Single-Patient-Use Only

REFRIGERATE / DO NOT FREEZE

For subcutaneous use / Rx only

Needles not included

Becton, Dickinson and Company pen needles are recommended for use with this device

www.forteo.com

Lilly

PACKAGE LABEL

PACKAGE LABEL – FORTEO 20 mcg per dose, 2.24 mL

NDC 0002-9678-01

Do NOT transfer contents to a syringe

ATTENTION PHARMACIST: Medication Guide and device User Manual for patient inside carton

MS8400

FORTEO®

teriparatide injection

20 mcg per dose (given once daily subcutaneously)

Each single-patient-use prefilled pen will deliver 28 subcutaneous doses.

560 mcg/ 2.24 mL (250 mcg/mL)

For Single-Patient-Use Only

REFRIGERATE / DO NOT FREEZE

For subcutaneous use / Rx only

Needles not included

Becton, Dickinson and Company pen needles are recommended for use with this device

www.forteo.com

Lilly